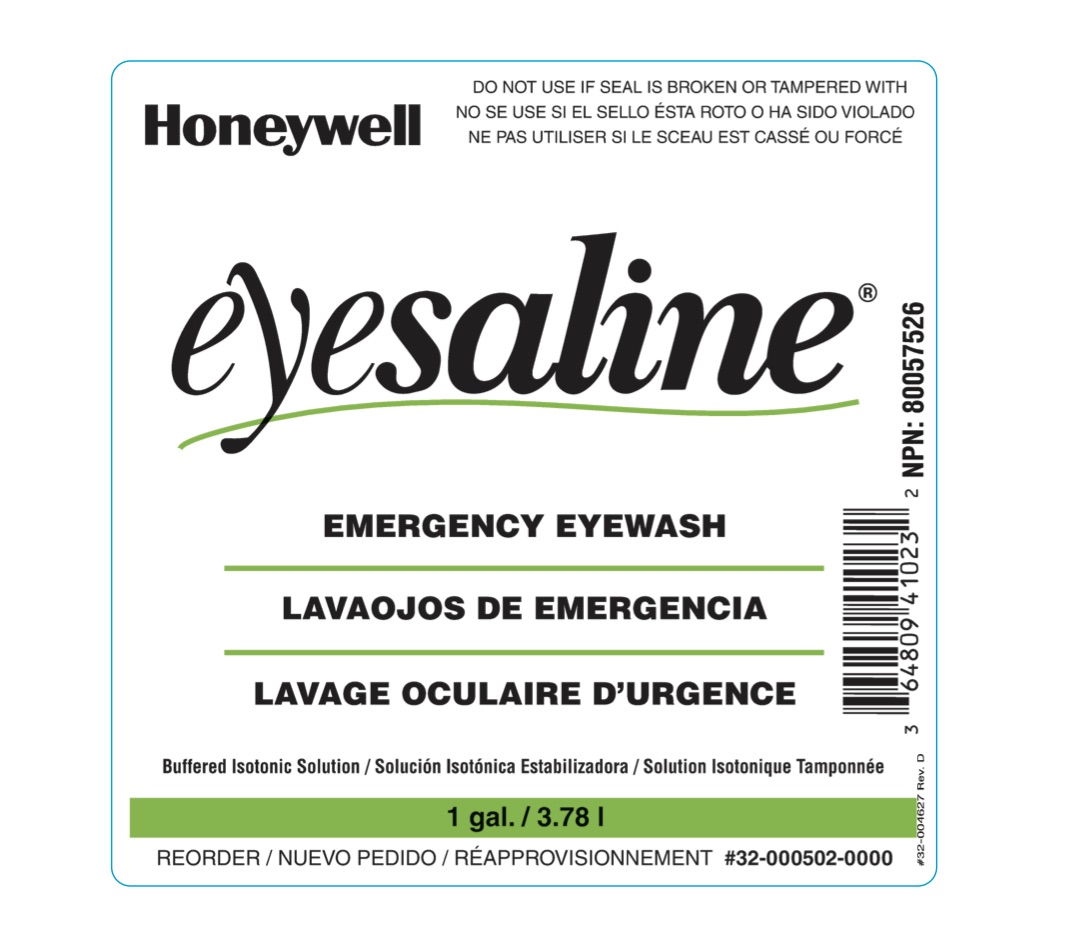 DRUG LABEL: Sperian Eyesaline Emergency Eyewash
NDC: 64809-100 | Form: LIQUID
Manufacturer: Sperian Eye & Face Protection Inc
Category: otc | Type: HUMAN OTC DRUG LABEL
Date: 20180321

ACTIVE INGREDIENTS: WATER 98.6 mL/100 mL
INACTIVE INGREDIENTS: SODIUM CHLORIDE; SODIUM PHOSPHATE, MONOBASIC, MONOHYDRATE; SODIUM PHOSPHATE, DIBASIC; EDETATE DISODIUM; BENZALKONIUM CHLORIDE

Sperian Eyesaline Emergency Eyewash

Active ingredient

Purified Water 98.6%

Purpose

Emergency eyewash

Uses

- For flushing or irrigating the eye to reduce chances of severe injury caused by acid, alkali, or particulate contamination

Warnings

For external use only- Obtain immediate medical treatment for all open wounds in or near eyes. To avoid contamination, do not touch tip of container to any surface. Do not reuse. Once opened, discard.

Do not use

- if solution changes color or gets cloudy
- with contact lenses
- if seal is broken or tampered with
- if the eye is lacerated or object is embedded

Stop use and ask a doctor if you have

- changes in vision
- eye pain
- continued redness or irritation of the eye or if the condition worsens or persists

Keep out of reach of children

If swallowed, get medical help or contact a Poison Control Center right away.

Directions

- remove contacts before using
- flush the affected area as needed
- if necessary, continue flushing with emergency eyewash or shower

Other information

- store at room temperature, 59o to 86oF (15o to 30oC)
- do not freeze

Inactive Ingredients

benzalkonium chloride, edatate disodium, sodium chloride, sodium phosphate dibasic, sodium phosphate monobasic

Questions?

Call 1-800-430-5490

Sperian Eye & Face Protection, Inc.

(a Honeywell Company)

825 East Highway 151

Platteville, WI 53818 USA